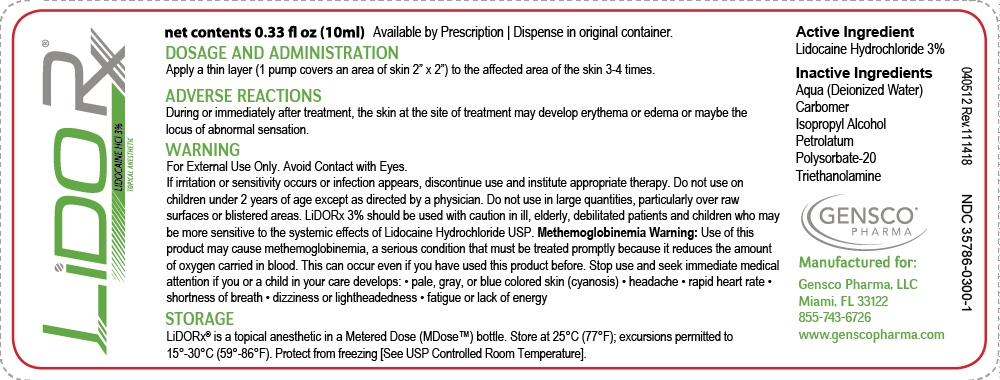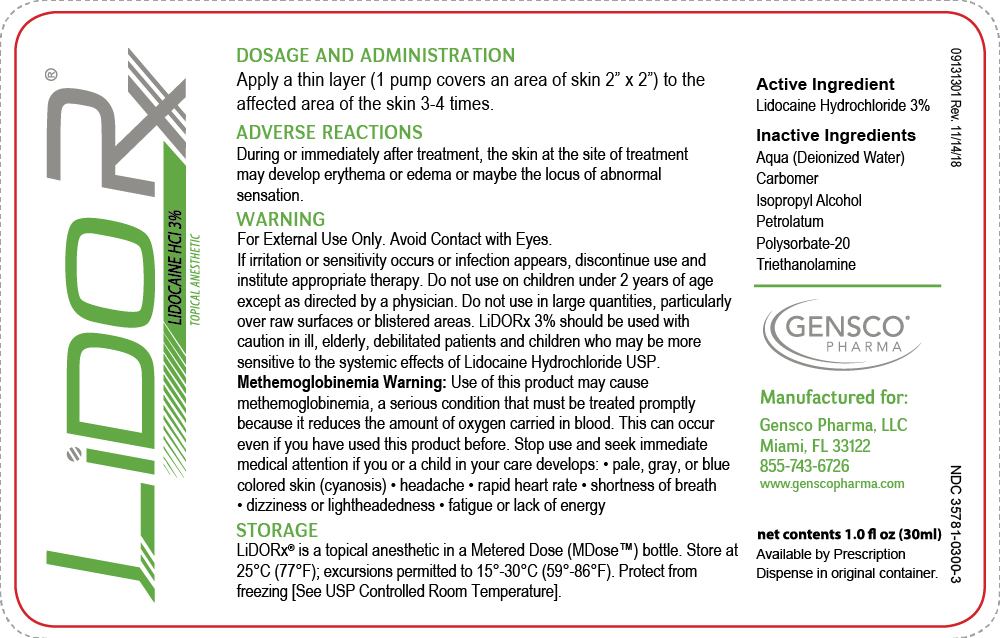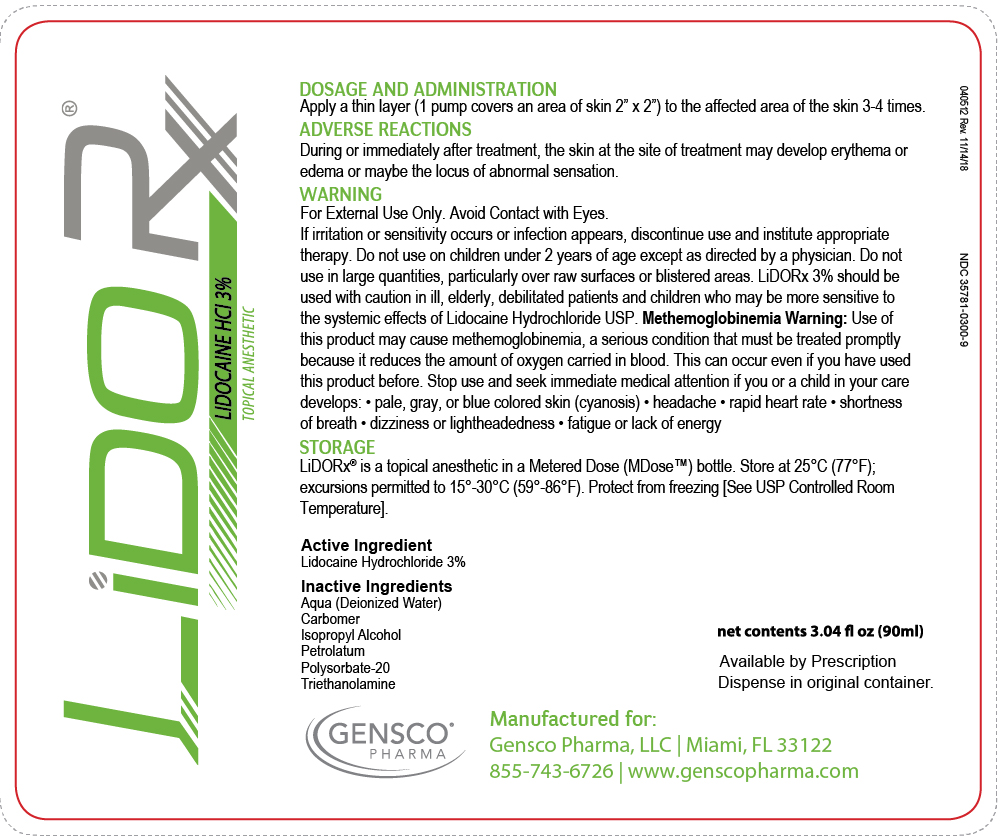 DRUG LABEL: Lido Rx
NDC: 35781-0300 | Form: GEL
Manufacturer: Gensco Laboratories, LLC
Category: prescription | Type: HUMAN PRESCRIPTION DRUG LABEL
Date: 20221004

ACTIVE INGREDIENTS: LIDOCAINE 30 mg/1 g
INACTIVE INGREDIENTS: WATER; CARBOMER COPOLYMER TYPE B (ALLYL PENTAERYTHRITOL CROSSLINKED); ISOPROPYL ALCOHOL; PETROLATUM; POLYSORBATE 20; TROLAMINE

HIGHLIGHTS OF PRESCRIBING INFORMATION

LiDORx
These highlights do not include all the information needed to use Lido see full prescribing information for safety and efficacy data and Initial U.S. Approval

Indications

These highlights do not include all the information needed to use Please see full prescription information

LiDORx® 3% is an Amide type Local Anesthetic indicated for:
Relief of pain, soreness, abrasions, minor burns, insect bites and discomfort due to pruritus, pruritic eczemas, pruritus ani, pruritus vulvae, hemorrhoids, anal fissures, and similar conditions of the skin and mucous membranes.

2. Dosage and Administration

Apply 1-4 pumps to the affected area three or four times daily not to exceed 16 pumps in twenty-four hours (24 Hrs) or as directed by a physician. As a topical anesthesic, apply an adequate amount for the desired procedure to the target area 10 minutes prior to initiation of procedure.

CONTRAINDICATIONS

Traumatized mucosa, secondary bacterial infection of the area of proposed
application and known hypersensitivity to any of the components.
Lidocaine Hydrochloride USP is contraindicated in patients with a known
history of hypersensitivity to local anesthetics of the amide type.

5. Warnings and Precautions

For External Use Only. Avoid Contact with Eyes.
If irritation or sensitivity occurs or infection appears, discontinue use and institute appropriate therapy.
LiDORx® 3% should be used with caution in ill, elderly, debilitated patients and children who may be more sensitive to the systemic effects
of Lidocaine Hydrochloride USP.
Methemoglobinemia Warning: Cases of methemoglobinemia have been reported in association with local anesthetic use. Although all patients are at risk for methemoglobinernia, patients with glucose-6-phosphate dehydrogenase deficiency, congenital or idiopathic methemoglobinemia, cardiac or pulmonary compromise, infants under 6 months of age, and concurrent exposure to oxidizing agents or their metabolites are more susceptible to developing clinical manifestations of the condition. If local anesthetics must be used in these patients, close monitoring for symptoms and signs of methemoglobinemia is recommended. Signs and symptoms of methemoglobinemia may occur immediately or may be delayed some hours after exposure and are characterized by a cyanotic skin discoloration and abnormal coloration of the blood. Methemoglobin levels may continue to rise; therefore, immediate treatment is required to avert more serious central nervous system and cardiovascular adverse effects, including seizures, coma, arrhythmias, and death. Discontinue LiDORx® and any other oxidizing agents. Depending on the severity of the symptoms, patients may respond to supportive care, i.e., oxygen therapy, hydration. More severe symptoms may require treatment with methylene blue, exchange transfusion, or hyperbaric oxygen.

6. Adverse Reactions

Most common adverse reactions are redness or swelling at the application site. Less common side effects, such as sluggishness,

confusion, slow breathing, low blood pressure, or slow heartbeat, may occur.

To report SUSPECTED ADVERSE REACTIONS, contact Gensco Pharma at 855-743-6726 or FDA at 1-800-FDA-1088 or www.fda.gov/medwatch.

7. Drug Interactions

Prilocaine, Bupivacaine, Amyl nitrates/ sodium nitrate/ sodium thiosulfate, Dofetilide, Iomitapide, Beta-blockers (eg, atenolol), Cimetidine, or Class 1 antiarrhythmic drugs (ex. Mexiletine). Patients that are administered local anesthetics may be at increased risk of developing methemoglobinernia when concurrently exposed to the following oxidizing agents: Nitrates/Nitrites (nitroglycerin, nitroprusside, nitric oxide, nitrous oxide); Local anesthetics (benzocaine, lidocaine, bupivacaine, inepivacaine, tetracaine, prilocaine, procaine, articaine, ropivacaine); Antineoplastic agents (cyclophospharnide, flutamide, rasburicase, ifosfarnide, hydroxyurea); Antibiotics (dapsone, sulfonamides, nitrofurantoin, para-arninosalicvlic acid); Antimalarials (chloroquine, primaquine); Anticonvulsants (phenytoin, sodium valproate, phenobarbital); Other drugs (acetaminophen, metoclopramide, sulfa drugs (i.e., sulfasalazine), quinine).
This may not be a complete list of all interactions that may occur. Ask your health care provider if LiDORx® 3% may interact with other
medicines that you take.

FULL PRESCRIBING INFORMATION

Indications

Anesthetic for relief of pain at site of injury; relief of musculoskeletal pain
and soreness; pain from neuropathy; local medical procedures,
injections and vaccines; relief of pruritis, pruritic eczema, abrasions,
minor burns, insect bites, pain, soreness and discomfort due to pruritis
ani, pruritis vulvae, hemorrhoids, anal fissures and similar conditions of
the skin and mucous membranes.

2. Dosage and Administration

Each pump of the LiDORx® 3% bottle (30mL Airless Pump bottle - NDC:35781-0300-3) will deliver 0.25 mL of LiDORx® 3% enough to cover
a 2 inch by 2 inch area of skin. A single application should not exceed 4 pumps of the Airless bottle, equal to 1 gram of LiDORx® 3%, (30 mg of
Lidocaine Hydrochloride USP).

No more than 16 pumps of the Airless Pump bottle, approximately 4 grams of LiDORx® 3% (120 mg Lidocaine Hydrochloride USP,) should be
administered in any one day.

Although the incidence of adverse effects with LiDORx® 3% is quite low,caution should be exercised, particularly when employing large amounts,
since the incidence of adverse effects is directly proportional to the total dose of local anesthetic agent administered.

2.1 Dosage for children

It is difficult to recommend a maximum dose of any drug for children since this varies as a function of age and weight. For children less
than ten years who have a normal lean body mass and a normal lean body development, the maximum dose may be determined by
the application of one of the standard pediatric drug formulas (e.g., Clark’s rule). For example a child of five years weighing 50 lbs., the
dose of lidocaine should not exceed 75-100 mg when calculated according to Clark’s rule. In any case, the maximum amount of
Lidocaine Hydrochloride USP administered should not exceed 4.3 mg/kg (2.0 mg/lb) of body weight.

2.2 Administration

Apply 1-4 pumps to the affected area three or four times daily not to exceed 16 pumps in twenty-four hours (24 Hrs) or as directed by a
physician. As a topical anesthesic, apply an adequate amount for the desired procedure to the target area 10 minutes prior to initiation
of procedure.

3. Dosage Form and Strength

LiDORx® 1% is a Topical Gel. Each gram of LiDORx® 1% contains 1% Lidocaine Hydrochloride USP (10mg). Lid10ml

LiDORx® 3% is a Topical Gel. Each gram of LiDORx® 3% contains 3% Lidocaine Hydrochloride USP (30mg). Lid30ml

LiDORx® 9% is a Topical Gel. Each gram of LiDORx® 9% contains 9% Lidocaine Hydrochloride USP (90mg). Lid90ml

CONTRAINDICATIONS

Lidocaine Hydrochloride USP is contraindicated in patients with a known history of hypersensitivity to local anesthetics of the amide type or to other components of LidoRx 3%.

Do not use LidoRx 3% on traumatized mucosa or in the presence of secondary bacterial infection of the area of proposed application.

5. Warnings and Precautions

If irritation or sensitivity occurs or infection appears, discontinue use and institute appropriate therapy. LiDORx® 3% Gel should be used with
caution in ill, elderly, debilitated patients and children who may be more sensitive to the systemic effects of Lidocaine Hydrochloride USP. In case
of accidental ingestion get medical help or contact poison control center right away.

Methemoglobinemia: Cases of methemoglobinemia have been reported in association with local anesthetic use. Although all patients
are at risk for methemoglobinernia, patients with glucose-6-phosphate dehydrogenase deficiency, congenital or idiopathic methemoglobinemia,
cardiac or pulmonary compromise, infants under 6 months of age, and concurrent exposure to oxidizing agents or their metabolites
are more susceptible to developing clinical manifestations of the condition. If local anesthetics must be used in these patients, close
monitoring for symptoms and signs of methemoglobinemia is recommended. Signs and symptoms of methemoglobinemia may
occur immediately or may be delayed some hours after exposure and are characterized by a cyanotic skin discoloration and abnormal
coloration of the blood. Methemoglobin levels may continue to rise; therefore, immediate treatment is required to avert more serious
central nervous system and cardiovascular adverse effects, including seizures, coma, arrhythmias, and death. Discontinue LiDORx® and
any other oxidizing agents. Depending on the severity of the symptoms, patients may respond to supportive care, i.e., oxygen
therapy, hydration. More severe symptoms may require treatment with methylene blue, exchange transfusion, or hyperbaric oxygen

6. Adverse Reactions

Adverse experiences following the administration of Lidocaine Hydrochloride USP are similar in nature to those observed with other amide local anesthetic agents. These adverse experiences are, in general, dose-related and may result from high plasma levels caused by excessive dosage or rapid absorption, or may result from a hypersensitivity, idiosyncrasy or diminished tolerance on the part of the patient.
Serious adverse experiences are generally systemic in nature. The following types are those most commonly reported:

6.1 Central Nervous System

CNS manifestations are excitatory and/or depressant and may be characterized by lightheadedness, nervousness, apprehension, euphoria, confusion, dizziness, drowsiness, tinnitus, blurred or double vision, vomiting, sensations of heat, cold or numbness, twitching, tremors, convulsions, unconsciousness, respiratory depression and arrest. The excitatory manifestations may be very brief or may not occur at all, in which case the first manifestation of toxicity may be drowsiness merging into unconsciousness and respiratory arrest. Drowsiness following
the administration of Lidocaine Hydrochloride USP is usually an early sign of a high blood level of the drug and may occur as a
consequence of rapid absorption.

6.2 Cardiovascular system

Cardiovascular manifestations are usually depressant and are characterized by bradycardia, hypotension, and cardiovascular collapse, which may lead to cardiac arrest.

6.3 Allergic

Allergic reactions are characterized by cutaneous lesions, urticaria, edema or anaphylactoid reactions. Allergic reactions may occur as a result of sensitivity either to the local anesthetic agent or to other components in the formulation. Allergic reactions as a result of sensitivity to Lidocaine Hydrochloride USP are extremely rare and, if they occur, should be managed by conventional means. The detection of sensitivity by skin testing is of doubtful value.

7. Drug Interactions

7.1 Serious interactions:

Antiarrhythmic Drugs: LiDORx® 3% should be used with caution in patients receiving Class I antiarrhythmic drugs (such as tocainide and mexiletine) since the toxic effects are additive and potentially synergistic.

Bupivacaine liposome: Lidocaine Hydrochloride USP increases toxicity of Bupivacaine by increasing the free (unencapsulated)bupiacaine.
Dofetilide: Lidocaine Hydrochloride USP increases effects of dofetilide thru pharmacodynamic synergism.
Lomitapide: Lidocaine Hydrochloride USP increases levels of lomitapide by affecting hepatic/intestinal enzymes CYP3A4 metabolism.

7.2 General interactions: DRUG INTERACTIONS: Patients that are administered local anesthetics may be at increased risk of developing methemoglobinemia when concurrently exposed to the following oxidizing agents:

Class | Examples
Nitrates/Nitrites | Nitroglycerin, Nitroprusside, nitric oxide, nitrous oxide
Local anesthetics | Benzocaine, Lidocaine, Bupivacaine, Mepivacaine, Letracaine, prilocaine, procaine, articaine, ropivacaine
Antincoplastic agents | cyclophosphosphamide,flutamide, rasburicase, ifosfamide, hydroxyurea
Antibiotics | Dapsone, sulfonamides, nitrofurantoin,paraaminosalicylic acid
Antimalarials | Chloroquine,primaquine
Anticonvulsants | phenytoin,sodium valproate,phenobarbital
Other drugs | acetaminophen, metoclopramide, sulfa drugs (i.e, Sulfasalazine), quinine

Drugs metabolized via CYP3A4 enzyme: (ex. Antipsychotics, SSRIs, TCAs, many chemotherapeutics, calcium channel bockers, benzodiazopines) Lidocaine Hydrochloride USP may increase serum levels of many drugs metabolized by hepatic / intestinal CYP3A4 enzymes.

Drugs that affect hepatic CYP1A2 enzyme: (ex. Quinoline antibiotics, cimetidine, barbiturates, benzodiazepines, erythromycin) May increase serum Lidocaine Hydrochloride USP levels by decreasing Lidocaine Hydrochloride USP metabolism by CYP1A2 enzyme.

8. Use in Specific Populations

8.1 Use in Pregnancy

Teratogenic Effects. Pregnancy Category B. Reproduction studies have been performed in rats at doses up to 6.6 times the human dose and have revealed no evidence of harm to the fetus caused by Lidocaine Hydrochloride USP. There are, however, no adequate and well-controlled studies in pregnant women. Animal reproduction studies are not always predictive of human response. General consideration should be given to this fact before administering Lidocaine Hydrochloride USP to women of childbearing potential, especially during early pregnancy when maximum organogenesis takes place.

8.2 Labor and Delivery

Lidocaine Hydrochloride USP is not contraindicated in labor and delivery. Should LiDORx® 3% be used concomitantly with other products containing Lidocaine Hydrochloride USP, the total dose contributed by all formulations must be kept in mind. 8.3 Nursing Mothers: It is not known whether this drug is excreted in human milk. Because many drugs are excreted in human milk, caution should be exercised when Lidocaine
Hydrochloride USP. is administered to a nursing woman.

8.4 Pediatric use

Dosage in children should be reduced, commensurate with age, body weight and physical condition. Caution must be taken to avoid over dosage when applying LiDORx® 3% to large areas of injured or abraded skin, since the systemic absorption of Lidocaine Hydrochloride USP may be
increased under such conditions.

8.5 Geriatric use

No overall clinical differences in safety or effectiveness have been observed between the healthy elderly and other adult patients.

9. Over Dosage

Acute emergencies from local anesthetics are generally related to high
plasma levels encountered during therapeutic use of local anesthetics.
(see ADVERSE REACTIONS, WARNINGS, and PRECAUTIONS).

9.1 Management of local anesthetic emergencies

The first consideration is prevention, best accomplished by careful and constant monitoring of cardiovascular and respiratory vital signs and the patient’s state of consciousness after each local anesthetic administration. At the first sign of change, oxygen should be administered. The first step in the management of convulsions consists of immediate attention to the maintenance of a patent airway and assisted or controlled ventilation with oxygen and a delivery system capable of permitting immediate positive airway pressure by mask. Immediately after the institution of these ventilatory measures, the adequacy of the circulation should be evaluated, keeping in mind that drugs used to treat convulsions sometimes depress the circulation when administered intravenously. Should convulsions persist despite adequate respiratory support, and if the status of the circulation permits, small increments of an ultra-short acting barbiturate (such as thiopental or thiamylal) or a benzodiazepine (such as diazepam) may be administered intravenously. The clinician should be familiar, prior to use of local anesthetics, with these anticonvulsant drugs. Supportive treatment of circulatory depression may require administration of intravenous fluids and, when appropriate, a vasopressor as directed by the clinical situation (e.g., ephedrine). If not treated immediately, both convulsions and cardiovascular depression can result in hypoxia, acidosis, bradycardia, arrhythmias and cardiac arrest. If cardiac arrest should occur, standard cardiopulmonary resuscitative measures should be instituted. Dialysis is of negligible value in the treatment of acute over dosage with Lidocaine Hydrochloride USP The oral LD50 of Lidocaine HCI USP in non-fasted female rats is 459 (346-773) mg/kg (as the salt) and 214 (159-324) mg/kg (as the salt) in fasted female rats.

10. Description

10.1 Active Ingredients

Each gram of LiDORx® 3% contains Lidocaine Hydrochloride USP 3% (30 mg). Lidocaine Hydrochloride USP is chemically designated as acetamide, 2- (diethylamino)-N-(2,6-dimethylphenyl), and has the following structure.

10.2 Inactive Ingredients

AQUA (DEIONIZED WATER),
CARBOMER, ISOPROPYL ALCOHOL, PETROLATUM,
POLYSORBATE-20, TRIETHANOLAMINE.

11. Clinical Pharmacology

11.1 Mechanism of action

LiDORx® 3% releases Lidocaine Hydrochloride USP from a mild acidic vehicle to stabilize the neuronal membrane by inhibiting the ionic fluxes required for initiation and conduction of impulses, thereby effecting local anesthetic action. A mild acidic vehicle lowers pH to increase protection against alkaline irritations and to provide a favorable environment for healing.

11.2 Onset and duration of anesthesia

LiDORx® 3% effects local, topical anesthesia. The onset is 3-5 minutes. Clinical testing has demonstrated the average onset of anesthesia occurs 5 to 10 minutes after application of LiDORx® 3%. In a study evaluating the onset and duration of anesthesia in 37 healthy volunteers the average time to anesthesia was 8 minutes and 40 seconds while duration of anesthesia in the majority of subjects was between 8-15 minutes (median 10 minutes and 46 seconds). There was considerable inter-subject variation that may be due to subject age and relative skin condition.

11.3 Hemodynamics

Excessive blood levels may cause changes in cardiac output, total peripheral resistance, and mean arterial pressure. These changes may be attributable to a direct depressant effect of the local anesthetic agent on various components of the cardiovascular system.

11.4 Pharmacokinetics and metabolism

Lidocaine Hydrochloride USP may be absorbed following topical administration to mucous membranes or open wounds, its rate and extent of absorption depending upon the specific site of application, duration of exposure, concentration, and total dosage. In general, the rate of absorption of local anesthetic agents following topical application occurs most rapidly after intratracheal administration. Lidocaine Hydrochloride USP is also well-absorbed from the gastrointestinal tract, but little intact drug appears in the circulation because of biotransformation in the liver. Lidocaine Hydrochloride USP is metabolized rapidly by the liver, and metabolites and unchanged drug are excreted by the kidneys. Biotransformation includes oxidative N-dealkylation, ring hydroxylation, cleavage of the amide linkage, and conjugation. N-dealkylation, a major pathway of biotransformation, yields the metabolites monoethylglycinexylidide and glycinexylidide. The pharmacological/toxicological actions of
these metabolites are similar to, but less potent than, those of Lidocaine Hydrochloride USP. Approximately 90% of Lidocaine Hydrochloride USP administered is excreted in the form of various metabolites, and less than 10% is excreted unchanged. The primary metabolite in urine is a conjugate of 4-hydroxy-2,6-dimethylaniline. The plasma binding of Lidocaine Hydrochloride USP is dependent on drug concentration, and the fraction bound decreases with increasing concentration. At concentrations of 1 to 4 μg of free base per mL, 60 to 80 percent of Lidocaine Hydrochloride USP is protein bound. Binding is also dependent on the plasma concentration of the alpha-l-acid glycoprotein. Lidocaine Hydrochloride USP crosses the blood-brain and placental barriers, presumably by passive diffusion. Studies of Lidocaine Hydrochloride USP metabolism following intravenous bolus injections have shown that the elimination half-life of this agent is typically 1.5 to 2.0 hours. Because of the rapid rate at which Lidocaine Hydrochloride USP is metabolized, any condition that affects liver function may alter Lidocaine Hydrochloride USP kinetics. The half-life may be prolonged two-fold or more in patients with liver dysfunction. Renal dysfunction does not affect Lidocaine Hydrochloride USP kinetics but may increase the accumulation of metabolites. Factors such as acidosis and the use of CNS stimulants and depressants affect the CNS levels of Lidocaine Hydrochloride USP required to produce overt systemic effects. Objective adverse manifestations become increasingly apparent with increasing venous plasma levels above 6.0 μg free base per mL. In the rhesus monkey arterial blood levels
of 18-21 μg/mL have been shown to be threshold for convulsive activity.

12. Non-Clinical Toxicity

Studies of Lidocaine Hydrochloride USP in animals to evaluate the carcinogenic and mutagenic potential or the effect on fertility have not been conducted

13. How Supplied / Storage and Handling

HOW SUPPLIED

LiDORx® 3% (Lidocaine HCl USP 3%): 0.33 oz (9.5g) 10mL Airless Pump - NDC 35781-0300-1; 1.01 oz (28.5g) 30mL Airless Pump - NDC 35781-0300-3; 3.04 oz (86g) 90mL Airless Pump - NDC 35781-0300-9.

STORE AND DISPOSE OF THIS AND ALL MEDICATIONS OUT OF REACH OF CHILDREN AND PETS.

All prescriptions using this product shall be pursuant to state statutes as applicable. This product may be administered under a physician’s supervision. There are no implied or explicit claims on the therapeutic equivalence. Store at 25ºC (77ºF); excursions permitted to 15º-30ºC
(59º-86º F). See USP Controlled Room Temperature. Protect from freezing.

Manufactured for:
Gensco Pharma
8550 NW 33rd Street
Miami, FL 33122.

14. Patient Counseling Information

Inform patients that use of local anesthetics may cause methemoglobinemiia, a serious condition that must be treated promptly. Advise patients or caregivers to stop use and seek immediate medical attention if they or someone in their care experience the following signs or symptoms: pale, gray, or blue colored skin (cyanosis); headache; rapid heart rate; shortness of breath; lightheadedness or fatique.

What is LiDORx® 3%?
LiDORx® 3% is a topical gel containing 3% lidocaine HCl USP (30mg /gram of gel). Lidocaine Hydrochloride USP is a local anesthetic (numbing medication). It works by blocking nerve signals in your body. LiDORx® 3% (for use on the skin) is used to reduce pain or discomfort caused by skin irritations such as sunburn, insect bites, poison ivy, poison oak, poison sumac, and minor cuts, scratches, hemorrhoids, and burns. LiDORx® 3% may also be used for purposes not listed in this medication guide.

How do I use LiDORx® 3%?
Use exactly as prescribed by your doctor. Do not use in larger or smaller amounts or for longer than recommended. Follow the directions on your
prescription label. LiDORx® 3% is generally for use on the skin only. If your medication comes with patient instructions for safe and effective use, follow these directions carefully. Ask your doctor or pharmacist if you have any questions. Your body may absorb more of this medication if you use too much, if you apply it over large skin areas, or if you apply heat, bandages, or plastic wrap to treated skin areas. Skin that is cut or irritated may also absorb more topical medication than healthy skin. Use the smallest amount of this medication needed to numb the skin or relieve pain. Do not use large amounts of LiDORx® 3%, or cover treated skin areas with a bandage or plastic wrap without medical advice. Be
aware that many cosmetic procedures are performed without a medical doctor present. LiDORx® 3% may be applied with your finger tips or a
cotton swab. Follow your doctor’s instructions. Do not apply this medication to swollen skin areas or deep puncture wounds. Avoid using the medicine on skin that is raw or blistered, such as a severe burn or abrasion. Store at room temperature away from moisture and heat. Keep both used and unused LiDORx® 3% out of the reach of children or pets. The amount of Lidocaine Hydrochloride USP in the gel could be harmful to a child or pet who accidentally sucks on or swallows the gel. Seek emergency medical attention if this happens.

What happens if I miss a dose?

Since LiDORx® 3% is used as needed, you may not be on a dosing schedule. If you are using the medication regularly, use the missed dose as soon as you remember. Skip the missed dose if it is almost time for your next scheduled dose. Do not use extra medicine to make up the missed dose.

What happens if I overdose?
Seek emergency medical attention or call the Poison Help line at 1-800-222-1222. LiDORx® 3% applied to the skin is not likely to cause an overdose unless you apply more than the recommended dose. Overdose may also occur if you apply heat, bandages, or plastic wrap to treated skin areas. Improper use of LiDORx® 3% may result in death. Overdose symptoms may include drowsiness, confusion, nervousness, ringing in your ears, blurred vision, feeling hot or cold, numbness, muscle twitches, uneven heartbeats, seizure (convulsions), slowed breathing, or respiratory failure (breathing stops).

What should I avoid while using LiDORx® 3%?
Do not allow this medication to come into contact with your eyes. If it does, rinse with water. Avoid using other topical medications on the affected area unless directed by a physician.

LiDORx® 3% side effects:
Get emergency medical help if you have any of these signs of an allergic reaction: hives; difficulty breathing; swelling of your face, lips, tongue, or throat.

Use of local anesthetics may cause methemoglobinemia, a serious condition that must be treated promptly. Patients or caregivers should stop use and seek immediate medical attention if they or someone in their care experience the following signs or symptoms: pale, gray, or blue colored skin (cyanosis); headache; rapid heart rate; shortness of breath; lightheadedness; or fatigue.

Stop using LiDORx® 3% and call your doctor at once if you have any of these serious side effects:
• uneven heartbeats;
• drowsiness, confusion;
• tremors, seizure (convulsions); or
• blurred vision.
Less serious side effects include:
• mild irritation, redness, or swelling where the medication isapplied; or
• numbness in places where the medicine is accidentally applied.

This is not a complete list of side effects and others may occur. Call your doctor for medical advice about side effects. You may report side effects
to FDA at 1-800-FDA-1088.

PREGNANCY and BREAST-FEEDING:
It is not known if Lidocaine Hydrochloride USP can cause harm to the fetus. If you become pregnant, contact your doctor. You will need to discuss the benefits and risks of using LiDORx® 3% while you are pregnant. It is not known if Lidocaine Hydrochloride USP is found in breast milk after topical use. If you are or will be breast-feeding while you use LiDORx® 3%, check with your doctor. Discuss any possible risks to your baby.

Lidocane HCL

1. Lido Rx 10 ml

2. Lido Rx 30 ml

3. Lido Rx 90 ml